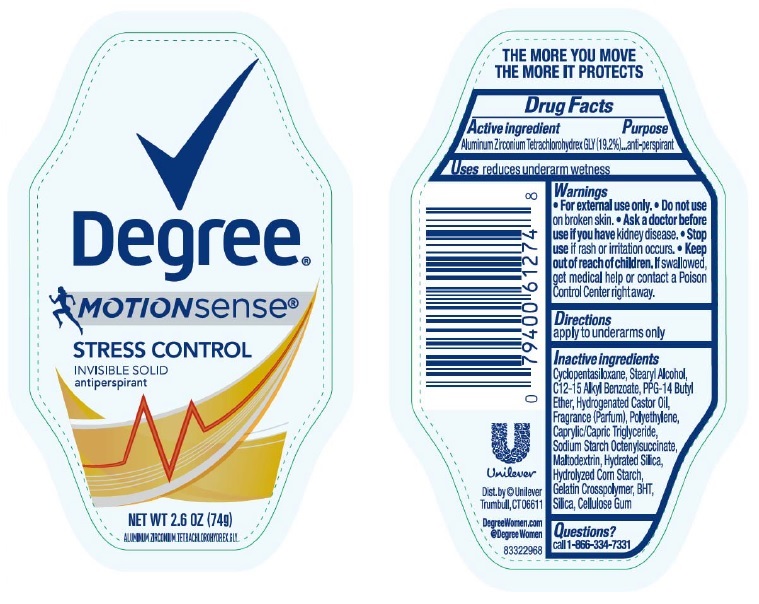 DRUG LABEL: Degree
NDC: 64942-1481 | Form: STICK
Manufacturer: Conopco, Inc. d/b/a/ Unilever
Category: otc | Type: HUMAN OTC DRUG LABEL
Date: 20161109

ACTIVE INGREDIENTS: ALUMINUM ZIRCONIUM TETRACHLOROHYDREX GLY 19.2 g/100 g
INACTIVE INGREDIENTS: CYCLOMETHICONE 5; STEARYL ALCOHOL; ALKYL (C12-15) BENZOATE; PPG-14 BUTYL ETHER; HYDROGENATED CASTOR OIL; HIGH DENSITY POLYETHYLENE; MEDIUM-CHAIN TRIGLYCERIDES; MALTODEXTRIN; HYDRATED SILICA; STARCH, CORN; BUTYLATED HYDROXYTOLUENE; SILICON DIOXIDE; CARBOXYMETHYLCELLULOSE SODIUM, UNSPECIFIED FORM

Degree Motionsense Stress Control Invisible Solid Antiperspirant

Active Ingredient

Aluminum Zirconium Tetrachlorohydrex GLY(19.2%)

Purpose

anti-perspirant

Uses

reduces underarm wetness

Warnings

- For external use only.
- Do not use on broken skin.
- Ask a doctor before using if you have kidney disease.
- Stop use if rash or irritation occurs.

• Keep out of reach of children. If swallowed, get medical help or contact a Poison Control Center right away.

Directions

apply to underarms only.

Inactive Ingredients

Cyclopentasiloxane, Stearyl Alcohol, C12-15 Alkyl Benzoate, PPG-14 Butyl Ether, Hydrogenated Castor Oil, Fragrance (Parfum), Polyethylene, Caprylic/Capric Triglyceride, Sodium Starch Octenylsuccinate, Maltodextrin, Hydrated Silica, Hydroylzed Corn Starch, Gelatin Crosspolymer, BHT, Silica, Cellulose Gum

Questions?

Call toll-free 1-866-334-7331

INVISIBLE SOLID antiperspirant

THE MORE YOU MOVE THE MORE IT PROTECTS